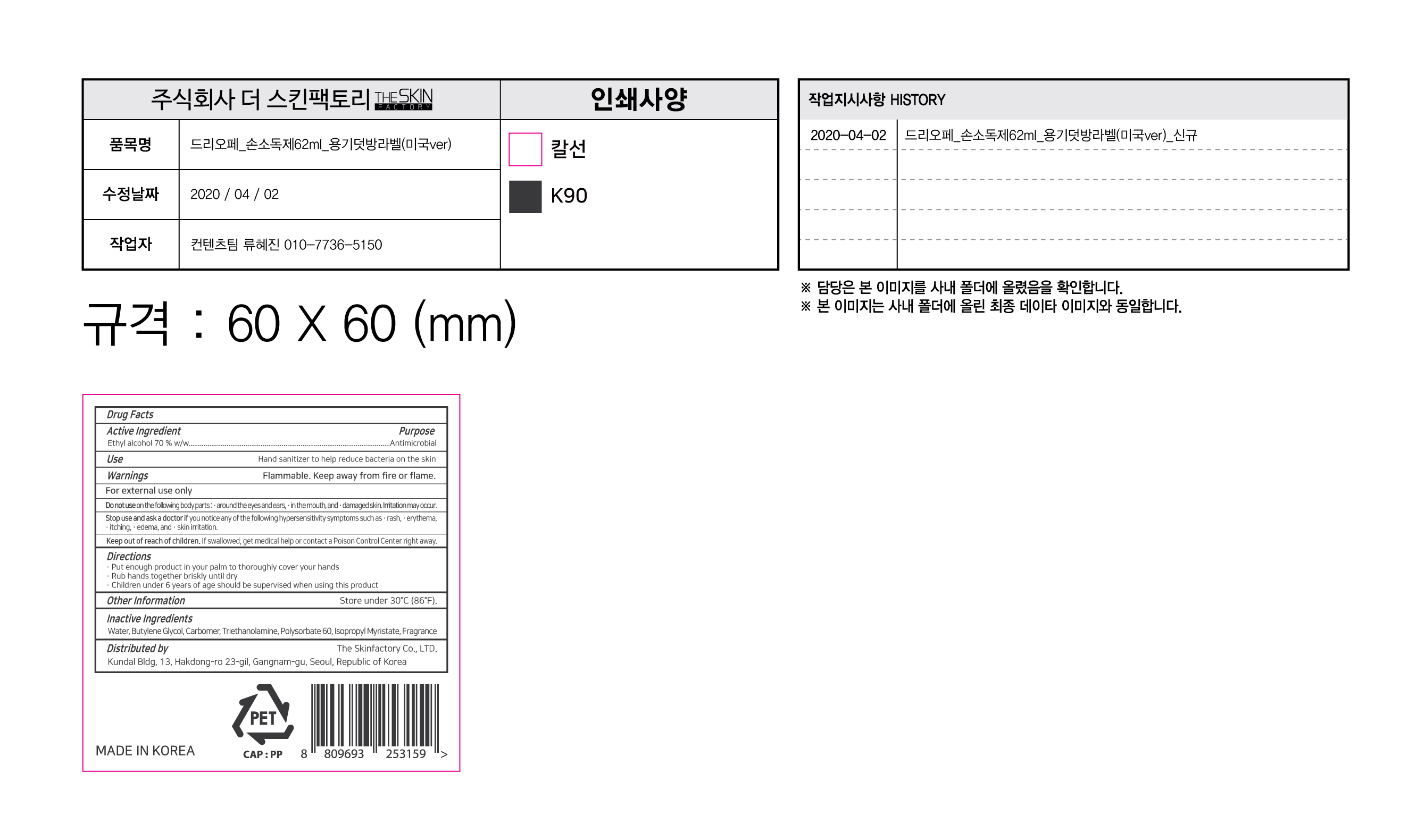 DRUG LABEL: DRYOPE FRESH PURE HAND
NDC: 74773-0002 | Form: GEL
Manufacturer: THESKINFACTORY Co., Ltd.
Category: otc | Type: HUMAN OTC DRUG LABEL
Date: 20200406

ACTIVE INGREDIENTS: ALCOHOL 70 g/100 mL
INACTIVE INGREDIENTS: BUTYLENE GLYCOL; WATER

Drug Facts

ACTIVE INGREDIENT

Alcohol

INACTIVE INGREDIENT

Glycerin, Carbomer, etc.

PURPOSE

Antiseptic

KEEP OUT OF REACH OF THE CHILDREN

INDICATIONS AND USAGE

For the external use only

WARNINGS

For external use only.

Flammable, keep away from fire or flame.

When using this product keep out of eyes. If contact with eyes occurs, rinse promptly and thoroughly with water.

Stop use and ask a doctor if significant irritation or sensitization develops.

Keep out of reach of children. If swallowed, get medical help or contact a Poison Control Center right away.

DOSAGE AND ADMINISTRATION

Put enough product in your palm to thoroughly cover your hands.

Rub your hands together briskly until dry.

Chidren under 6 years of age should be supervised when using this product.